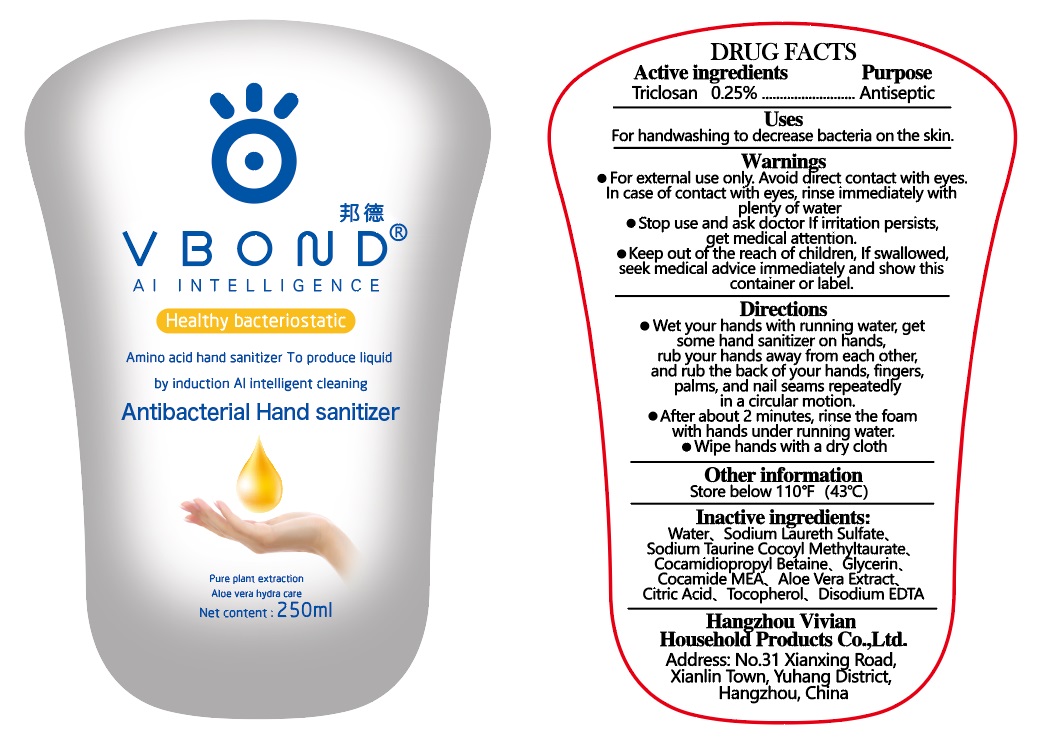 DRUG LABEL: Antibacterial Hand Sanitizer
NDC: 80155-102 | Form: LIQUID
Manufacturer: HangZhou Vivian Household Products Co.,Ltd
Category: otc | Type: HUMAN OTC DRUG LABEL
Date: 20200923

ACTIVE INGREDIENTS: TRICLOSAN 2.5 mg/1 mL
INACTIVE INGREDIENTS: water; SODIUM LAURETH SULFATE; GLYCERIN; ALOE VERA LEAF; EDETATE DISODIUM; TOCOPHEROL

hand sanitizer

Active ingredient

Triclosan 0.25%

Purpose

Antiseptic

USE

For handwashing to decrease bacteria on the skin.

Warnings

For external use only.

When using this product

Avoid direct contact with eyes. In case of contact with eyes, rinse immediately with plenty of water

Stop use and ask a doctor

- If irritation persists, get medical attention.

Keep out of reach of children.

If swallowed, seek medical advice immediately and show this container or label.

Directions

- Wet your hands with running water, get some hand sanitizer on hands, rub your hands away from each other, and rub the back of your hands, fingers, palms, and nail seams repeatedly in a circular motion.
- After about 2 minutes, rinse the foam with hands under running water.
- Wipe hands with a dry cloth

Other Information:

Store below 110℉（43℃）

Inactive ingredients

Water、Sodium Laureth Sulfate、Sodium Taurine Cocoyl Methyltaurate、Cocamidiopropyl Betaine、Glycerin、Cocamide MEA、Aloe Vera Extract、Citric Acid、Tocopherol、Disodium EDTA